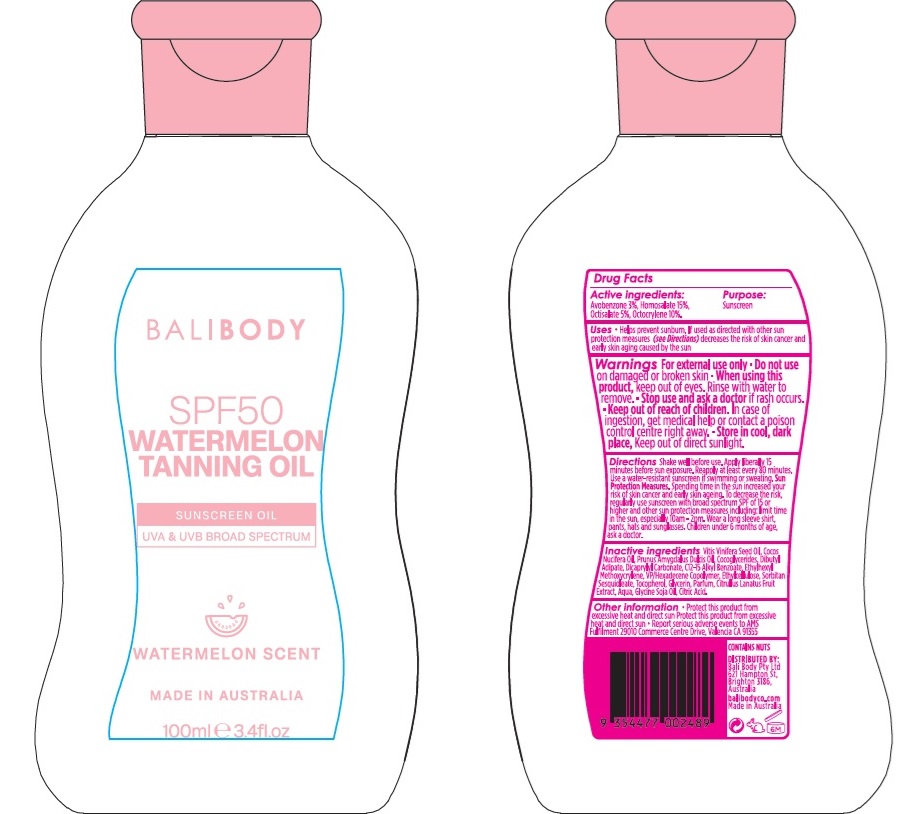 DRUG LABEL: Bali Body Watermelon Tanning Oil SPF 50
NDC: 70630-0036 | Form: OIL
Manufacturer: Bali Body Pty Ltd
Category: otc | Type: HUMAN OTC DRUG LABEL
Date: 20240816

ACTIVE INGREDIENTS: OCTISALATE 50 mg/1 mL; AVOBENZONE 30 mg/1 mL; HOMOSALATE 150 mg/1 mL; OCTOCRYLENE 100 mg/1 mL
INACTIVE INGREDIENTS: ETHYLCELLULOSE, UNSPECIFIED; SORBITAN SESQUIOLEATE; CITRIC ACID MONOHYDRATE; COCONUT OIL; DICAPRYLYL CARBONATE; ALKYL (C12-15) BENZOATE; GLYCERIN; WATERMELON; WATER; GRAPE SEED OIL; VINYLPYRROLIDONE/HEXADECENE COPOLYMER; SOYBEAN OIL; ALMOND OIL; COCO-GLYCERIDES; DIBUTYL ADIPATE; ETHYLHEXYL METHOXYCRYLENE; TOCOPHEROL

Bali Body Watermelon Tanning Oil SPF 50

Active ingredients

Avobenzone 3%

Homosalate 15%

Octisalate 5%

Octocrylene 10%

Purpose

Sunscreen

Uses

- Helps prevent sunburn. If used as directed with other sun protection measures (see Directions) decreases the risk of skin cancer and early skin aging caused by the sun

Warnings

For external use only

Do not use

on damaged or broken skin

When using this product

keep out of eyes. Rinse with water to remove.

Stop use and ask a doctor

if rash occurs.

Keep out of reach of children.

In case of ingestion, get medical help or contact a poison control centre right away. Store in cool, dark place, Keep out of direct sunlight.

Directions

Shake well before use. Apply liberally 15 minutes before sun exposure. Reapply at least every 80 minutes. Use a water-resistant sunscreen if swimming or sweating. Sun Protection Measures. Spending time in the sun increased your risk of skin cancer and early skin ageing. To decrease the risk, regularly use sunscreen with broad spectrum SPF of 15 or higher and other sun protection measures including: limit time in the sun, especially 10am - 2 pm. Wear a long sleeve shirt, pants, hats and sunglasses. Children under 6 months of age, ask a doctor.

Inactive ingredients

Vitis Vinifera Seed Oil, Cocos Nucifera Oil, Prunus Amygdalus Dulcis Oil, Cocoglycerides, Dibutyl Adipate, Dicaprylyl Carbonate, C12-15 Alkyl Benzoate, Ethylhexyl Methoxycrylene, VP/Hexadecene Copolymer, Ethylcellulose, Sorbitan Sesquioleate, Tocopherol, Glycerin, Parfum, Citrullus Lanatus Fruit Extract, Aqua, Glycine Soja Oil, Citric Acid.

Other information

- Protect this product from excessive heat and direct sun.
- Report serious adverse events to AMS Fulfilment 29010 Commerce Centre Drive, Valencia CA 91355